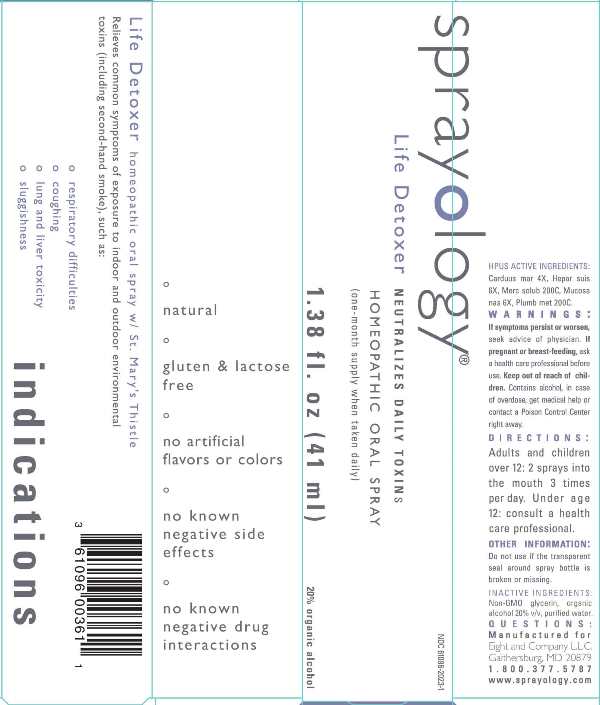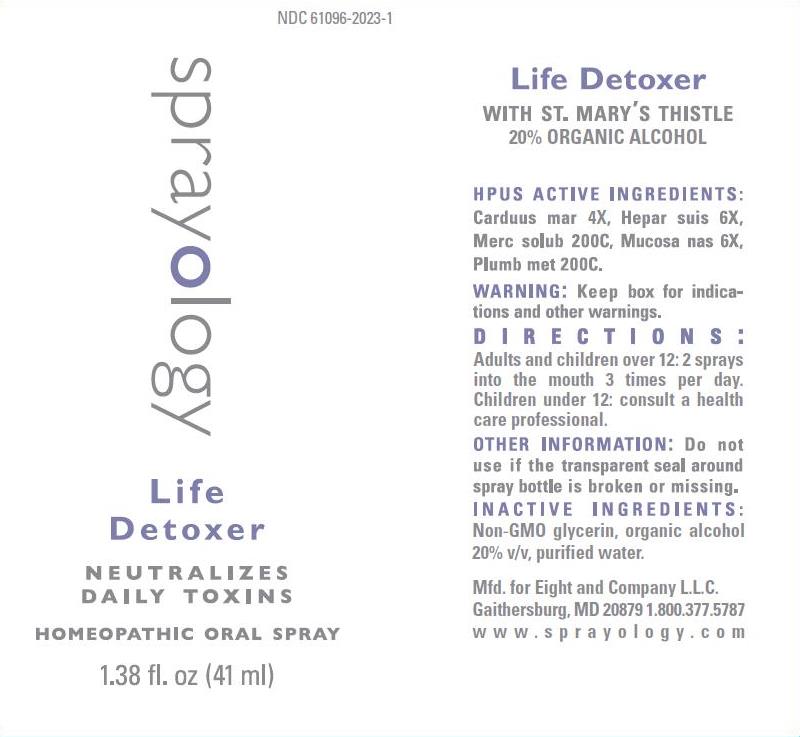 DRUG LABEL: Life Detoxer
NDC: 61096-2023 | Form: LIQUID
Manufacturer: Eight and Company L.L.C
Category: homeopathic | Type: HUMAN OTC DRUG LABEL
Date: 20251222

ACTIVE INGREDIENTS: MILK THISTLE 4 [hp_X]/41 mL; PORK LIVER 6 [hp_X]/41 mL; MERCURIUS SOLUBILIS 200 [hp_C]/41 mL; SUS SCROFA NASAL MUCOSA 6 [hp_X]/41 mL; LEAD 200 [hp_C]/41 mL
INACTIVE INGREDIENTS: GLYCERIN; ALCOHOL; WATER

Life Detoxer

ACTIVE INGREDIENTS:

Carduus mar 4X, Hepar suis 6X, Merc solub 200C, Mucosa nas 6X, Plumb met 200C

PURPOSE:

Relieves common symptoms of exposure to indoor and outdoor environmental toxins (including second-hand smoke), such as:

° respiratory difficulties
° coughing
° lung and liver toxicity
° sluggishness

WARNINGS:

If symptoms persist or worsen, seek advice of physician. If pregnant or breast-feeding, ask a health care professional before use. Keep out of reach of children. Contains alcohol, in case of overdose, get medical help or contact a Poison Control Center right away.

Keep out of reach of children. Contains alcohol, in case of overdose, get medical help or contact a Poison Control Center right away.

DIRECTIONS:

Adults and children over 12: 2 sprays into the mouth 3 times per day.
Under age 12: consult a health care professional.

OTHER INFORMATION:

Do not use if the transparent seal around spray bottle is broken or missing.

INDICATIONS:

Relieves common symptoms of exposure to indoor and outdoor environmental toxins (including second-hand smoke), such as:

° respiratory difficulties

° coughing

° lung and liver toxicity

° sluggishness

° natural

° gluten & lactose free

° no artificial flavors or colors

° no known negative side effects

° no known negative drug interactions

INACTIVE INGREDIENTS:

Non-GMO Glycerin, organic alcohol 20% v/v, purified water.

QUESTIONS:

Mfd. for Eight and Company L.L.C.

Gaithersburg, MD 20879 1.800.377.5787

www.sprayology.com

PACKAGE LABEL DISPLAY:

NDC 61096-2023

sprayology

Life Detoxer

NEUTRALIZES DAILY TOXINS

HOMEOPATHIC ORAL SPRAY

1.38 fl.oz (41 ml)